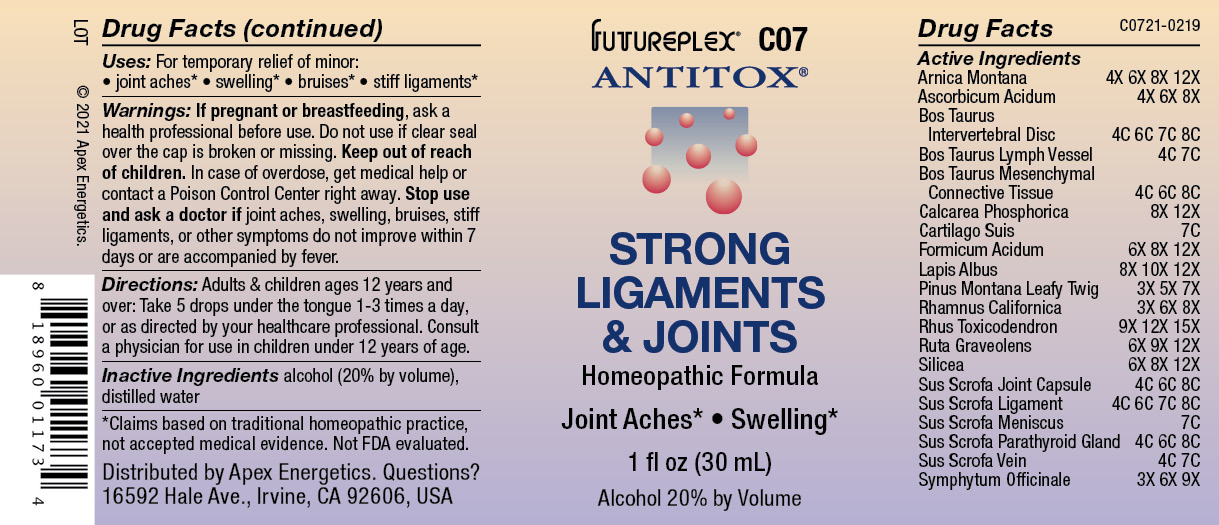 DRUG LABEL: C07
NDC: 63479-0307 | Form: SOLUTION/ DROPS
Manufacturer: Apex Energetics Inc.
Category: homeopathic | Type: HUMAN OTC DRUG LABEL
Date: 20240108

ACTIVE INGREDIENTS: SILICON DIOXIDE 12 [hp_X]/1 mL; SUS SCROFA LIGAMENT 8 [hp_C]/1 mL; SUS SCROFA MENISCUS 7 [hp_C]/1 mL; SUS SCROFA PARATHYROID GLAND 8 [hp_C]/1 mL; SUS SCROFA VEIN 7 [hp_C]/1 mL; TOXICODENDRON PUBESCENS LEAF 15 [hp_X]/1 mL; ARNICA MONTANA 12 [hp_X]/1 mL; BOS TAURUS MESENCHYME 8 [hp_C]/1 mL; BOS TAURUS LYMPH VESSEL 7 [hp_C]/1 mL; BOS TAURUS INTERVERTEBRAL DISC 8 [hp_C]/1 mL; TRIBASIC CALCIUM PHOSPHATE 12 [hp_X]/1 mL; SUS SCROFA CARTILAGE 7 [hp_C]/1 mL; FORMIC ACID 12 [hp_X]/1 mL; CALCIUM HEXAFLUOROSILICATE 12 [hp_X]/1 mL; PINUS MUGO LEAFY TWIG 7 [hp_X]/1 mL; ASCORBIC ACID 8 [hp_X]/1 mL; SUS SCROFA JOINT CAPSULE 8 [hp_C]/1 mL; COMFREY ROOT 9 [hp_X]/1 mL; FRANGULA CALIFORNICA BARK 8 [hp_X]/1 mL; RUTA GRAVEOLENS FLOWERING TOP 12 [hp_X]/1 mL
INACTIVE INGREDIENTS: WATER; ALCOHOL

C07

Active Ingredients
Arnica Montana | 4X 6X 8X 12X
Ascorbicum Acidum | 4X 6X 8X
Bos Taurus Intervertebral Disc | 4C 6C 7C 8C
Bos Taurus Lymph Vessel | 4C 7C
Bos Taurus Mesenchymal Connective Tissue | 4C 6C 8C
Calcarea Phosphorica | 8X 12X
Cartilago Suis | 7C
Formicum Acidum | 6X 8X 12X
Lapis Albus | 8X 10X 12X
Pinus Montana Leafy Twig | 3X 5X 7X
Rhamnus Californica | 3X 6X 8X
Rhus Toxicodendron | 9X 12X 15X
Ruta Graveolens | 6X 9X 12X
Silicea | 6X 8X 12X
Sus Scrofa Joint Capsule | 4C 6C 8C
Sus Scrofa Ligament | 4C 6C 7C 8C
Sus Scrofa Meniscus | 7C
Sus Scrofa Parathyroid Gland | 4C 6C 8C
Sus Scrofa Vein | 4C 7C
Symphytum Officinale | 3X 6X 9X

INDICATIONS AND USAGE

Uses:

For temporary relief of minor:

joint aches*

swelling*

bruises*

stiff ligaments*

*Claims based on traditional homeopathic practice, not accepted medical evidence. Not FDA evaluated.

WARNINGS

PREGNANCY OR BREAST FEEDING

If pregnant or breastfeeding, ask a health professional before use.

Do not use if clear seal over the cap is broken or missing.

Keep out of reach of children. In case of overdose, get medical help or contact a Poison Control Center right away.

Stop use and ask a doctor if joint aches, swelling, bruises, stiff ligaments, or other symptoms do not improve within 7 days or are accompanied by fever.

Directions:

Adults & children ages 12 years and over: Take 5 drops under the tongue 1-3 times a day, or as directed by your healthcare professional. Consult a physician for use in children under 12 years of age.

Inactive Ingredients

alcohol (20% by volume), distilled water

Distributed by Apex Energetics. Questions?

16592 Hale Ave., Irvine, CA 92606, USA

PACKAGE LABEL

FUTUREPLEX® C07

ANTITOX®

STRONG LIGAMENTS & JOINTS

Homeopathic Formula

Joint Aches*

Swelling*

1 fl oz (30 mL)

Alcohol 20% by Volume